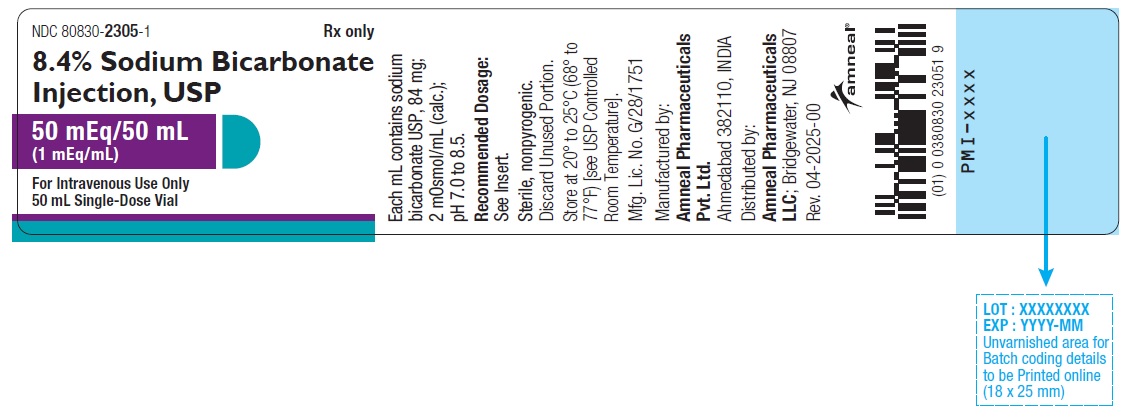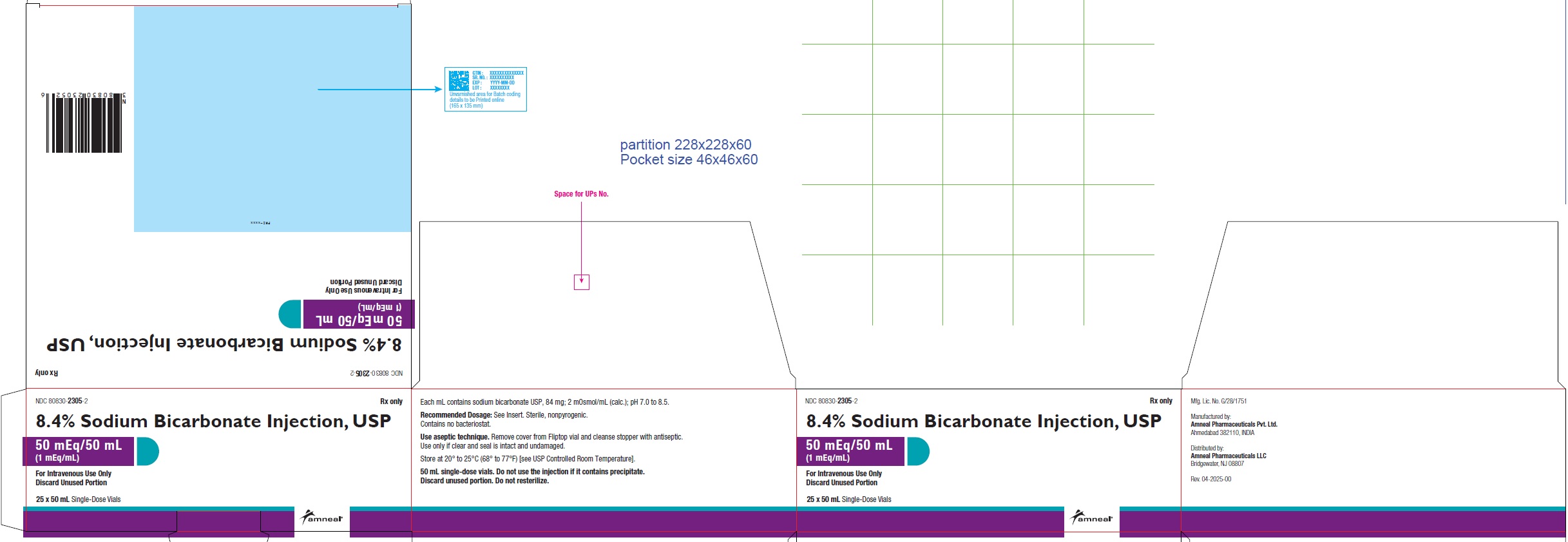 DRUG LABEL: SODIUM BICARBONATE
NDC: 80830-2305 | Form: INJECTION, SOLUTION
Manufacturer: Amneal Pharmaceuticals Private Limited
Category: prescription | Type: HUMAN PRESCRIPTION DRUG LABEL
Date: 20260120

ACTIVE INGREDIENTS: SODIUM BICARBONATE 84 mg/1 mL
INACTIVE INGREDIENTS: WATER

Sodium Bicarbonate Injection, USP
FOR CORRECTION OF METABOLIC ACIDOSIS AND OTHER CONDITIONS REQUIRING SYSTEMIC ALKALINIZATION.
Rx only

DESCRIPTION

Sodium bicarbonate injection, USP is a sterile, nonpyrogenic, hypertonic solution of sodium bicarbonate (NaHCO3) in water for injection for administration by the intravenous route as an electrolyte replenisher and systemic alkalizer.

Solution is offered in concentration of 8.4%. See table in HOW SUPPLIED section for contents and characteristics.

The solution contains no bacteriostat, antimicrobial agent or added buffer and are intended only for use as a single-dose injection, the approximate pH of the solution is between 7.0 to 8.5. When smaller doses are required, the unused portion should be discarded.

Sodium bicarbonate USP, 84 mg is equal to one milliequivalent each of Na^+ and HCO3^-. Sodium bicarbonate, USP is chemically designated NaHCO3, a white crystalline powder soluble in water and insoluble in ethanol.

Water for injection, USP is chemically designated H2O.

CLINICAL PHARMACOLOGY

Intravenous sodium bicarbonate therapy increases plasma bicarbonate, buffers excess hydrogen ion concentration, raises blood pH and reverses the clinical manifestations of acidosis.

Sodium bicarbonate in water dissociates to provide sodium (Na^+) and bicarbonate (HCO3^-) ions. Sodium (Na^+) is the principal cation of the extracellular fluid and plays a large part in the therapy of fluid and electrolyte disturbances. Bicarbonate (HCO3^-) is a normal constituent of body fluids and the normal plasma level ranges from 24 mEq/liter to 31 mEq/liter. Plasma concentration is regulated by the kidney through acidification of the urine when there is a deficit or by alkalinization of the urine when there is an excess. Bicarbonate anion is considered "labile" since at a proper concentration of hydrogen ion (H^+) it may be converted to carbonic acid (H2CO3) and thence to its volatile form, carbon dioxide (CO2) excreted by the lung. Normally a ratio of 1:20 (carbonic acid: bicarbonate) is present in the extracellular fluid. In a healthy adult with normal kidney function, practically all the glomerular filtered bicarbonate ion is reabsorbed; less than 1% is excreted in the urine.

INDICATIONS AND USAGE

Sodium bicarbonate injection is indicated in the treatment of metabolic acidosis which may occur in severe renal disease, uncontrolled diabetes, circulatory insufficiency due to shock or severe dehydration, extracorporeal circulation of blood, cardiac arrest and severe primary lactic acidosis. Sodium bicarbonate is further indicated in the treatment of certain drug intoxications, including barbiturates (where dissociation of the barbiturate-protein complex is desired), in poisoning by salicylates or methyl alcohol and in hemolytic reactions requiring alkalinization of the urine to diminish nephrotoxicity of hemoglobin and its breakdown products. Sodium bicarbonate also is indicated in severe diarrhea which is often accompanied by a significant loss of bicarbonate.

Treatment of metabolic acidosis should, if possible, be superimposed on measures designed to control the basic cause of the acidosis - e.g., insulin in uncomplicated diabetes, blood volume restoration in shock. But since an appreciable time interval may elapse before all of the ancillary effects are brought about, bicarbonate therapy is indicated to minimize risks inherent to the acidosis itself.

Vigorous bicarbonate therapy is required in any form of metabolic acidosis where a rapid increase in plasma total CO2 content is crucial - e.g., cardiac arrest, circulatory insufficiency due to shock or severe dehydration, and in severe primary lactic acidosis or severe diabetic acidosis.

CONTRAINDICATIONS

Sodium bicarbonate injection is contraindicated in patients who are losing chloride by vomiting or from continuous gastrointestinal suction, and in patients receiving diuretics known to produce a hypochloremic alkalosis.

WARNINGS

Solutions containing sodium ions should be used with great care, if at all, in patients with congestive heart failure, severe renal insufficiency and in clinical states in which there exists edema with sodium retention.

In patients with diminished renal function, administration of solution containing sodium ions may result in sodium retention.

The intravenous administration of this solution can cause fluid and/or solute overloading resulting in dilution of serum electrolyte concentrations, overhydration, congested states or pulmonary edema.

Extravascular infiltration should be avoided, see ADVERSE REACTIONS.

PRECAUTIONS

General

Do not use unless solution is clear and the container or seal is intact. Discard unused portion.

The potentially large loads of sodium given with bicarbonate require that caution be exercised in the use of sodium bicarbonate in patients with congestive heart failure or other edematous or sodium-retaining states, as well as in patients with oliguria or anuria. See table in HOW SUPPLIED section for amounts of sodium present in solution.

Caution must be exercised in the administration of parenteral fluids, especially those containing sodium ions, to patients receiving corticosteroids or corticotropin.

Potassium depletion may predispose to metabolic alkalosis and coexistent hypocalcemia may be associated with carpopedal spasm as the plasma pH rises. These dangers can be minimized if such electrolyte imbalances are appropriately treated prior to or concomitantly with bicarbonate infusion.

Laboratory Tests

The aim of all bicarbonate therapy is to produce a substantial correction of the low total CO2 content and blood pH, but the risks of overdosage and alkalosis should be avoided. Hence, repeated fractional doses and periodic monitoring by appropriate laboratory tests are recommended to minimize the possibility of overdosage.

Drug Interactions

Additives may be incompatible; norepinephrine and dobutamine are incompatible with sodium bicarbonate solution.

The addition of sodium bicarbonate to parenteral solutions containing calcium should be avoided, except where compatibility has been previously established. Precipitation or haze may result from sodium bicarbonate-calcium admixtures. NOTE: Do not use the injection if it contains precipitate.

Additives may be incompatible. Consult with pharmacist, if available. When introducing additives, consult with pharmacist, if available. When introducing additives, use aseptic technique, mix thoroughly and do not store.

Pregnancy: Teratogenic Effects

Animal reproduction studies have not been conducted with sodium bicarbonate. It is also not known whether sodium bicarbonate can cause fetal harm when administered to a pregnant woman or can affect reproduction capacity. Sodium bicarbonate should be given to a pregnant woman only if clearly needed.

Pediatric

Rapid injection (10 mL/min) of hypertonic sodium bicarbonate injection solution into neonates and children under two years of age may produce hypernatremia, a decrease in cerebrospinal fluid pressure and possible intracranial hemorrhage. The rate of administration in such patients should therefore be limited to no more than 8 mEq/kg/day. A 4.2% solution may be preferred for such slow administration. In emergencies such as cardiac arrest, the risk of rapid infusion must be weighed against the potential for fatality due to acidosis.

Geriatric

Clinical studies of sodium bicarbonate injection did not include sufficient numbers of subjects aged 65 and over to determine whether they respond differently from younger subjects. Other reported clinical experience has not identified differences in responses between the elderly and younger patients. In general, dose selection for an elderly patient should be cautious, usually starting at the low end of the dosing range, reflecting the greater frequency of decreased hepatic, renal, or cardiac function and of concomitant disease or other drug therapy.

ADVERSE REACTIONS

Overly aggressive therapy with sodium bicarbonate injection can result in metabolic alkalosis (associated with muscular twitchings, irritability and tetany) and hypernatremia.

Inadvertent extravasation of intravenously administered hypertonic solutions of sodium bicarbonate have been reported to cause chemical cellulitis because of their alkalinity, with tissue necrosis, ulceration or sloughing at the site of infiltration. Prompt elevation of the part, warmth and local injection of lidocaine or hyaluronidase are recommended to reduce the likelihood of tissue sloughing from extravasated intravenous (I.V.) solutions.

OVERDOSAGE

Should alkalosis result, the bicarbonate should be stopped and the patient managed according to the degree of alkalosis present. 0.9% sodium chloride injection intravenous may be given; potassium chloride also may be indicated if there is hypokalemia. Severe alkalosis may be accompanied by hyperirritability or tetany and these symptoms may be controlled by calcium gluconate. An acidifying agent such as ammonium chloride may also be indicated in severe alkalosis. See WARNINGS and PRECAUTIONS.

DOSAGE AND ADMINISTRATION

Sodium bicarbonate injection is administered by the intravenous route.

In cardiac arrest, a rapid intravenous dose of one to two 50 mL vials (44.6 mEq to 100 mEq) may be given initially and continued at a rate of 50 mL (44.6 mEq to 50 mEq) every 5 minutes to 10 minutes if necessary (as indicated by arterial pH and blood gas monitoring) to reverse the acidosis. Caution should be observed in emergencies where very rapid infusion of large quantities of bicarbonate is indicated. Bicarbonate solutions are hypertonic and may produce an undesirable rise in plasma sodium concentration in the process of correcting the metabolic acidosis. In cardiac arrest, however, the risks from acidosis exceed those of hypernatremia.

In less urgent forms of metabolic acidosis, Sodium bicarbonate injection may be added to other intravenous fluids. The amount of bicarbonate to be given to older children and adults over a four-to-eight-hour period is approximately 2 mEq/kg to 5 mEq/kg of body weight - depending upon the severity of the acidosis as judged by the lowering of total CO2 content, blood pH and clinical condition of the patient. In metabolic acidosis associated with shock, therapy should be monitored by measuring blood gases, plasma osmolarity, arterial blood lactate, hemodynamics and cardiac rhythm. Bicarbonate therapy should always be planned in a stepwise fashion since the degree of response from a given dose is not precisely predictable. Initially an infusion of 2 mEq/kg to 5 mEq/kg body weight over a period of 4 hours to 8 hours will produce a measurable improvement in the abnormal acid-base status of the blood. The next step of therapy is dependent upon the clinical response of the patient. If severe symptoms have abated, then the frequency of administration and the size of the dose may be reduced.

In general, it is unwise to attempt full correction of a low total CO2 content during the first 24 hours of therapy, since this may be accompanied by an unrecognized alkalosis because of a delay in the readjustment of ventilation to normal. Owing to this lag, the achievement of total CO2 content of about 20 mEq/liter at the end of the first day of therapy will usually be associated with a normal blood pH. Further modification of the acidosis to completely normal values usually occurs in the presence of normal kidney function when and if the cause of the acidosis can be controlled. Values for total CO2 which are brought to normal or above normal within the first day of therapy are very likely to be associated with grossly alkaline values for blood pH, with ensuing undesired side effects.

Parenteral drug products should be inspected visually for particulate matter and discoloration prior to administration, whenever solution and container permit. See PRECAUTIONS.

HOW SUPPLIED

Sodium Bicarbonate Injection, USP is supplied in the following dosage form:

NDC Code: | Conc % | mg/mL; (NaHCO3) | mEq/mL; (Na^+) | mEq/mL; (HCO3^-) | mEq/Container size; (mL) | mOsmol
80830-2305-1; (Single-dose vial) | 8.4 | 84 | 1 | 1 | 50/50 | 2/mL

The 50 mL sodium bicarbonate injection vials are supplied as 25 vials per carton with a single package insert (NDC Code: 80830-2305-2).

Exposure of pharmaceutical products to heat should be minimized. Avoid excessive heat. Protect from freezing. Store at 20° to 25°C (68° to 77°F) [see USP Controlled Room Temperature].

To report SUSPECTED ADVERSE REACTIONS, contact Amneal Pharmaceuticals LLC at 1-877-835-5472 or FDA at 1-800-FDA-1088 or www.fda.gov/medwatch.

Manufactured by:

Amneal Pharmaceuticals Pvt. Ltd.

Ahmedabad 382110, INDIA

Distributed by:

Amneal Pharmaceuticals LLC

Bridgewater, NJ 08807

Rev. 04-2025-00

PRINCIPAL DISPLAY PANEL

NDC 80830-2305-1

8.4% Sodium Bicarbonate Injection USP, 50 mEq/50 mL (1 mEq/mL)

50 mL Single-Dose Vial Label

Rx only

Amneal Pharmaceuticals LLC

NDC 80830-2305-2

8.4% Sodium Bicarbonate Injection USP, 50 mEq/50 mL (1 mEq/mL)

25 x 50 mL Single-Dose Vials Carton Label

Rx only

Amneal Pharmaceuticals LLC